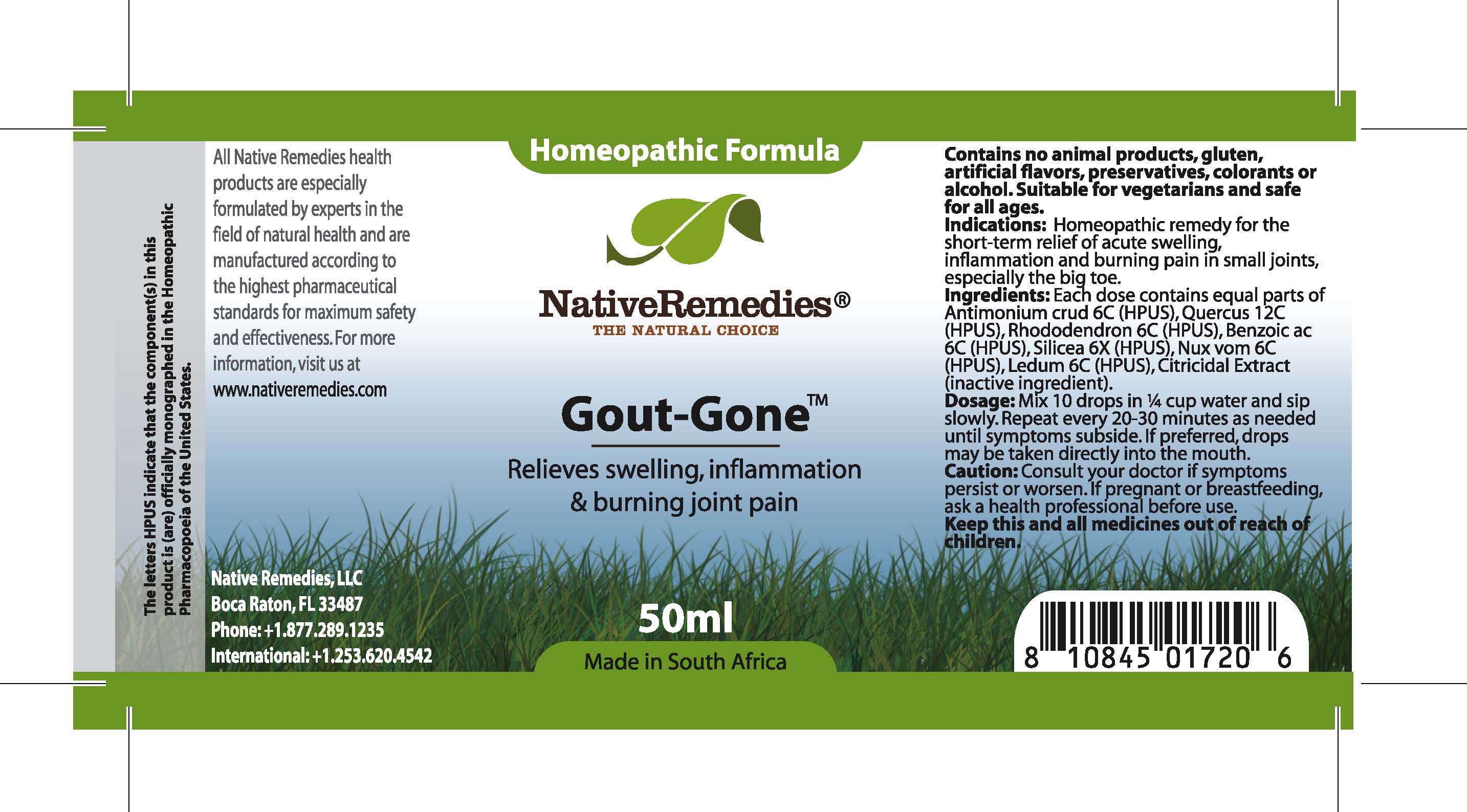 DRUG LABEL: Gout-Gone
NDC: 68647-168 | Form: TINCTURE
Manufacturer: Feelgood Health
Category: homeopathic | Type: HUMAN OTC DRUG LABEL
Date: 20110708

ACTIVE INGREDIENTS: ANTIMONY TRISULFIDE 6 [hp_C]/28.5 mL; CANDIDA PARAPSILOSIS 12 [hp_C]/28.5 mL; LEDUM PALUSTRE TWIG 6 [hp_C]/28.5 mL; 2-ETHYLHEXYL 4-PHENYLBENZOPHENONE-2'-CARBOXYLATE 6 [hp_C]/28.5 mL; SILICON DIOXIDE 6 [hp_X]/28.5 mL; STRYCHNOS NUX-VOMICA SEED 6 [hp_C]/28.5 mL; LEDUM PALUSTRE TWIG 6 [hp_C]/28.5 mL
INACTIVE INGREDIENTS: CITRUS PARADISI SEED 0.125 mL/50 mL; WATER 49.486 mL/50 mL

GOUT-GONE

PURPOSE

Relieves swelling, inflammation and burning joint pain

INDICATIONS AND USAGE

Indications: Homeopathic remedy for the relief of acute swelling, inflammation and burning pain in small joints, especially the big toe.

DOSAGE AND ADMINISTRATION

Dosage: Mix 10 drops in ¼ cup water and sip slowly. Repeat every 20-30 minutes as needed until symptoms subside. If preferred, drops may be taken directly into the mouth.

GENERAL PRECAUTIONS

Caution: Consult your doctor if symptoms persist or worsen. If pregnant or breastfeeding, ask a health professional before use. Keep this and all medicines out of reach of children.

ACTIVE INGREDIENT

Ingredients: Each dose contains equal parts of Antimonium crud (6C) (HPUS), Quercus (12C) (HPUS), Rhododendron (6C) (HPUS), Benzoic ac (6C) (HPUS), Silicea (6X) (HPUS), Nux vom (6C) (HPUS), Ledum (6C) (HPUS)

Citricidal Extract (inactive ingredient)

PREGNANCY

If pregnant or breastfeeding, ask a health professional before use.

WARNINGS

Contains no animal products, gluten, artificial flavors, preservatives, colorants or alcohol. Suitable for vegetarians and safe for all ages.

PATIENT COUNSELING INFORMATION

All Native Remedies health products are especially formulated by experts in the field of natural health and are manufactured according to the highest pharmaceutical standards for maximum safety and effectiveness. For more information, visit us at www.nativeremedies.com

Distributed by

Native Remedies, LLC

6531 Park of Commerce Blvd.

Suite 160

Boca Raton, FL 33487

Phone: 1.877.289.1235

International: + 1.561.999.8857

The letters HPUS indicate that the component(s) in this product is (are) officially monographed in the Homeopathic Pharmacopoeia of the United States.

KEEP OUT OF REACH OF CHILDREN

Keep this and all medications out of reach of children.